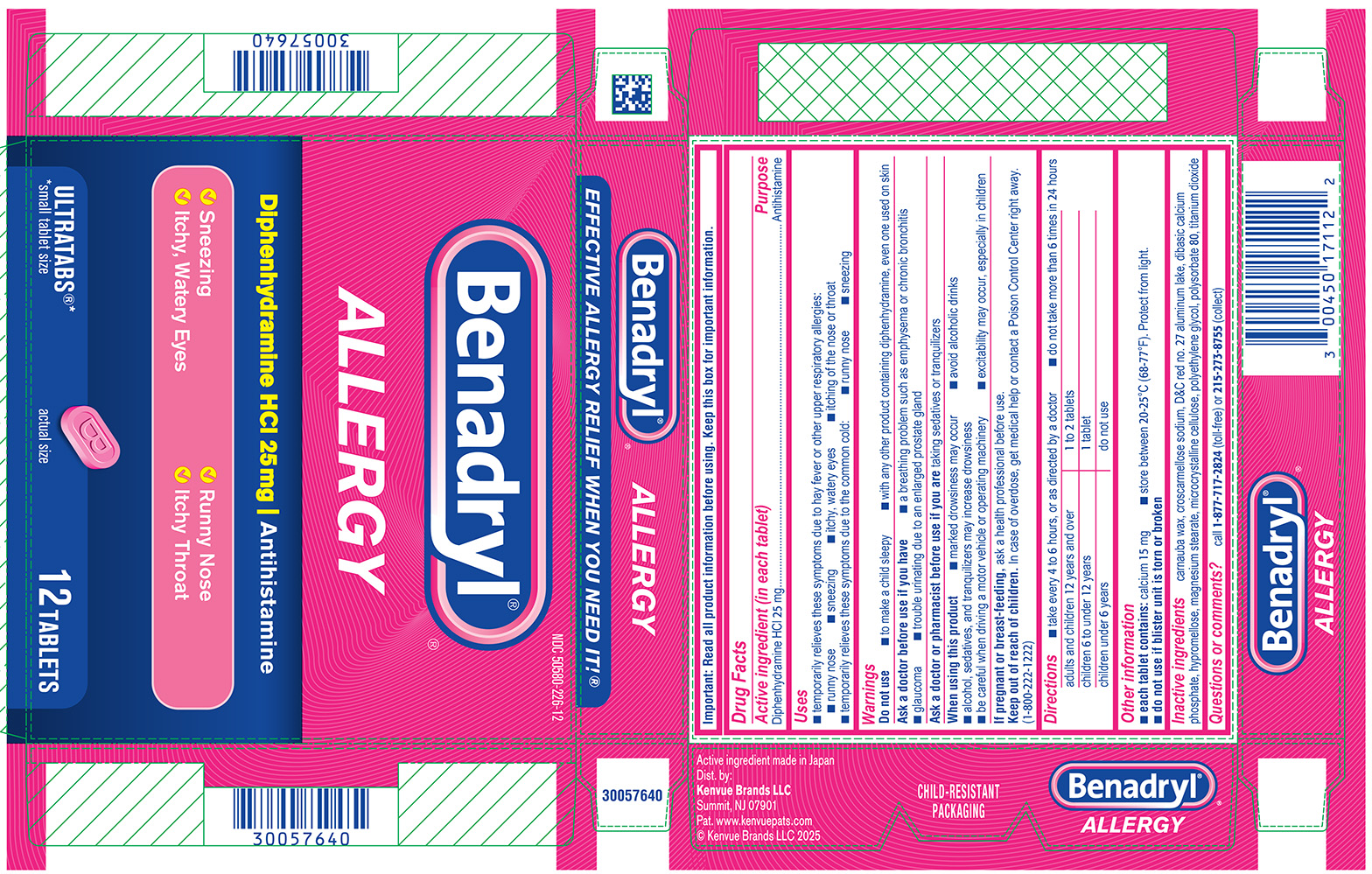 DRUG LABEL: Benadryl
NDC: 50580-226 | Form: TABLET, FILM COATED
Manufacturer: Kenvue Brands LLC
Category: otc | Type: HUMAN OTC DRUG LABEL
Date: 20260206

ACTIVE INGREDIENTS: DIPHENHYDRAMINE HYDROCHLORIDE 25 mg/1 1
INACTIVE INGREDIENTS: CARNAUBA WAX; CROSCARMELLOSE SODIUM; D&C RED NO. 27 ALUMINUM LAKE; DIBASIC CALCIUM PHOSPHATE DIHYDRATE; HYPROMELLOSE, UNSPECIFIED; MAGNESIUM STEARATE; MICROCRYSTALLINE CELLULOSE; POLYETHYLENE GLYCOL, UNSPECIFIED; POLYSORBATE 80; TITANIUM DIOXIDE

Benadryl®

Drug Facts

Active ingredient (in each tablet)

Diphenhydramine HCl 25 mg

Purpose

Antihistamine

Uses

- temporarily relieves these symptoms due to hay fever or other upper respiratory allergies:
  - runny nose
  - sneezing
  - itchy, watery eyes
  - itching of the nose or throat
- temporarily relieves these symptoms due to the common cold:
  - runny nose
  - sneezing

Warnings

Do not use

- to make a child sleepy
- with any other product containing diphenhydramine, even one used on skin

Ask a doctor before use if you have

- a breathing problem such as emphysema or chronic bronchitis
- glaucoma
- trouble urinating due to an enlarged prostate gland

Ask a doctor or pharmacist before use if you are taking sedatives or tranquilizers

When using this product

- marked drowsiness may occur
- avoid alcoholic drinks
- alcohol, sedatives, and tranquilizers may increase drowsiness
- be careful when driving a motor vehicle or operating machinery
- excitability may occur, especially in children

PREGNANCY OR BREAST FEEDING

If pregnant or breast-feeding, ask a health professional before use.

Keep out of reach of children. In case of overdose, get medical help or contact a Poison Control Center right away. (1-800-222-1222)

Directions

- take every 4 to 6 hours, or as directed by a doctor
- do not take more than 6 times in 24 hours

adults and children 12 years and over | 1 to 2 tablets
children 6 to under 12 years | 1 tablet
children under 6 years | do not use

Other information

- each tablet contains: calcium 15 mg
- store between 20-25°C (68-77°F). Protect from light.
- do not use if blister unit is torn or broken

Inactive ingredients

carnauba wax, croscarmellose sodium, D&C red no. 27 aluminum lake, dibasic calcium phosphate, hypromellose, magnesium stearate, microcrystalline cellulose, polyethylene glycol, polysorbate 80, titanium dioxide

Questions or comments?

call 1-877-717-2824 (toll-free) or 215-273-8755 (collect)

PRINCIPAL DISPLAY PANEL

NDC 50580-226-12

Benadryl®

ALLERGY

Diphenhydramine HCl 25mg | Antihistamine

✓ Sneezing
✓ Runny Nose
✓ Itchy, Watery Eyes
✓ Itchy Throat

ULTRATABS®*
*small tablet size

actual size

12 TABLETS